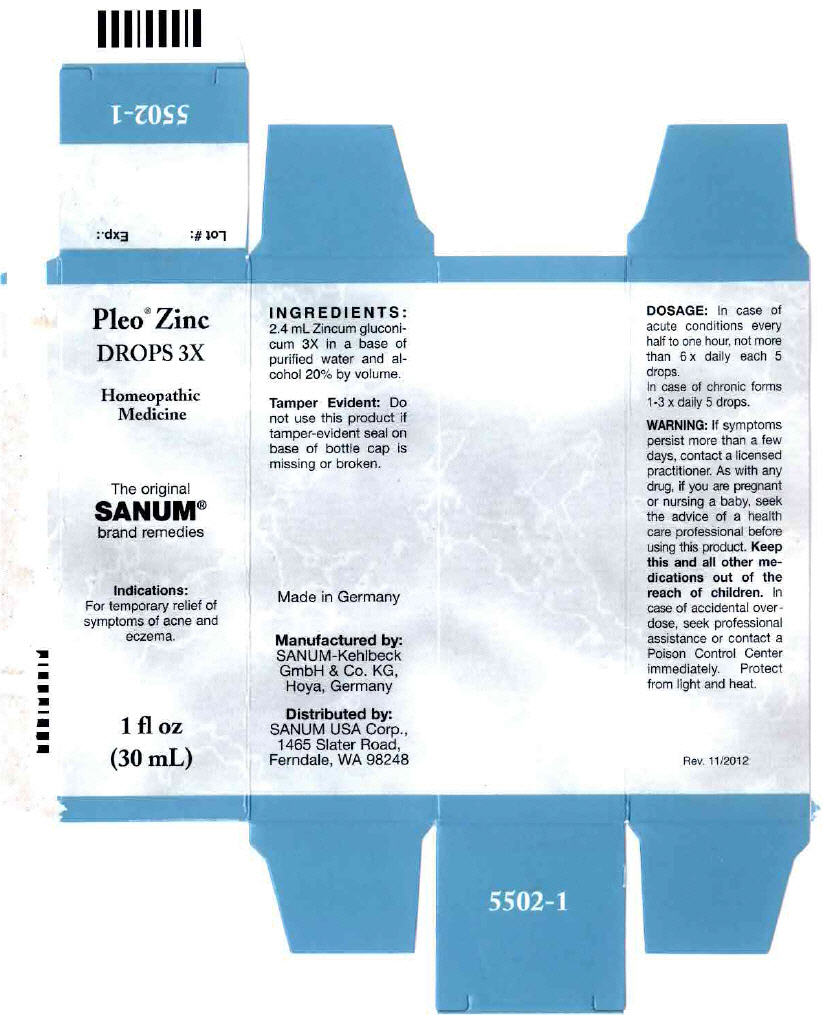 DRUG LABEL: Pleo Zinc
NDC: 60681-5502 | Form: SOLUTION/ DROPS
Manufacturer: Sanum Kehlbeck GmbH & Co. KG
Category: homeopathic | Type: HUMAN OTC DRUG LABEL
Date: 20130306

ACTIVE INGREDIENTS: zinc gluconate 3 [hp_X]/30 mL
INACTIVE INGREDIENTS: water; alcohol

Pleo® Zinc
DROPS 3X

Homeopathic Medicine

1 fl oz
(30 mL)

Indications

PURPOSE

For temporary relief of symptoms of acne and eczema.

INACTIVE INGREDIENT

INGREDIENTS

2.4 mL Zincum gluconicum 3X in a base of purified water and alcohol 20% by volume.

Tamper Evident

Do not use this product if tamper-evident seal on base of bottle cap is missing or broken.

DOSAGE

In case of acute conditions every half to one hour, not more than 6 × daily each 5 drops.

In case of chronic forms 1-3 × daily 5 drops.

WARNING

If symptoms persist more than a few days, contact a licensed practitioner. As with any drug, if you are pregnant or nursing a baby, seek the advice of a health care professional before using this product.

KEEP OUT OF REACH OF CHILDREN

Keep this and all other medications out of the reach of children. In case of accidental overdose, seek professional assistance or contact a Poison Control Center immediately.

STORAGE AND HANDLING

Protect fom light and heat.

Made in Germany

Distributed by:
SANUM USA Corp.
1465 Slater Road
Ferndale, WA 98248

Manufactured by:
Sanum-Kehlbeck
GmbH & Co. KG
Hoya, Germany

Rev. 03/2010

PRINCIPAL DISPLAY PANEL - 30 mL Bottle Carton

Pleo® Zinc
DROPS 3X

Homeopathic
Medicine

The original
SANUM®
brand remedies

Indications:
For temporary relief of
symptoms of acne and
eczema.

1 fl oz
(30 mL)